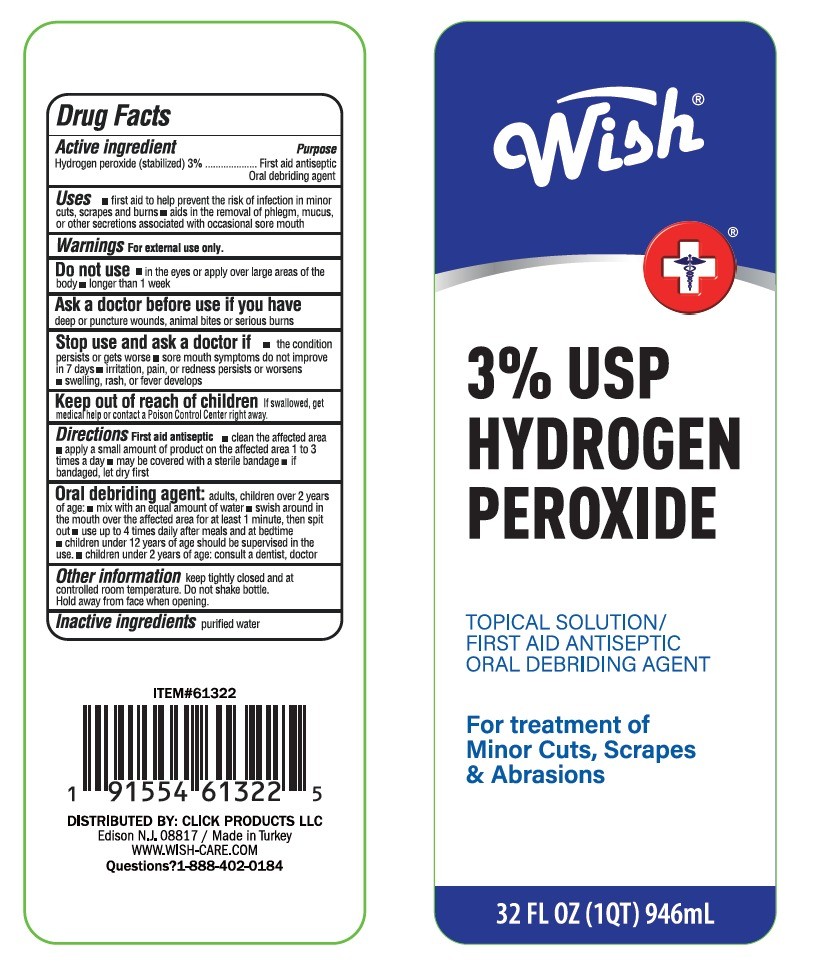 DRUG LABEL: WISH HYDROGEN PEROXIDE
NDC: 71611-081 | Form: LIQUID
Manufacturer: CLICK PRODUCTS LLC
Category: otc | Type: HUMAN OTC DRUG LABEL
Date: 20260112

ACTIVE INGREDIENTS: HYDROGEN PEROXIDE 283.8 mL/946 mL
INACTIVE INGREDIENTS: WATER 917.62 mL/946 mL

DOSAGE AND ADMINISTRATION

Directions

First aid antiseptic

clean the affected area

apply a small amount of product on the affected area 1 to 3 times a day

may be covered with a sterile bandalge

if bandaged, let dry first

Oral debriding agent

adults, children over 2 years of age

mix with an equal amount of water

swish around in the mounth over the affected area for at least 1 minute, then spit out

use up to 4 times daily after meals and at bedtime

children under 12 years of age should be supervised in the use

WARNINGS

For external use only

Do not use

in the eyes or apply over large areas of the body

longer than 1 week

Ask a doctor before use if you have

deep or puncture wounds, animal bites or serious burns

Stop use and ask a doctor if

the condition persists or gets worse
sore mouth symptoms do not imporive in 7 days

irritation, pain or reness persists or worsens

swelling, rash or fever develops

Keep out of reach of children

If swallowed, get medical help or contact a Poison Control Center right away

INACTIVE INGREDIENT

Inactive ingredients purified water

USES

First aid to help prevent the risk of infection in minor cuts, scrapes and burns

Aids in the removal of the phlegm, mucus, or other secretions associated with occasional sore mouth

KEEP OUT OF REACH OF CHILDREN

PURPOSE

First aid antiseptic oral debriding agent

Active ingredient

Hydrogen peroxide (stabilized) 3%

Purpose

First aid antiseptic oral debriding agent

USes

First aid to help prevent the risk of infection in minor cuts, scrapes and burns

Aids in the removal of the phlegm, mucus, or other secretions associated with occasional sore mouth

Warnings

For external use only

Do not use

in the eyes or apply over large areas of the body

longer than 1 week

Ask a doctor before use if you have

deep or puncture wounds, animal bites or serious burns

Stop use and ask a doctor if

the condition persists or gets worse
sore mouth symptoms do not imporive in 7 days

irritation, pain or reness persists or worsens

swelling, rash or fever develops

Keep out of reach of children

If swallowed, get medical help or contact a Poison Control Center right away

Directions

First aid antiseptic

clean the affected area

apply a small amount of product on the affected area 1 to 3 times a day

may be covered with a sterile bandalge

if bandaged, let dry first

Oral debriding agent

adults, children over 2 years of age

mix with an equal amount of water

swish around in the mounth over the affected area for at least 1 minute, then spit out

use up to 4 times daily after meals and at bedtime

children under 12 years of age should be supervised in the use

children under 2 years of age: consult a dentist, doctor

Other information keep tightly closed and ay controlled room temperature. Do not shake bottle

Hold away from face when opening

Inactive ingredients purified water